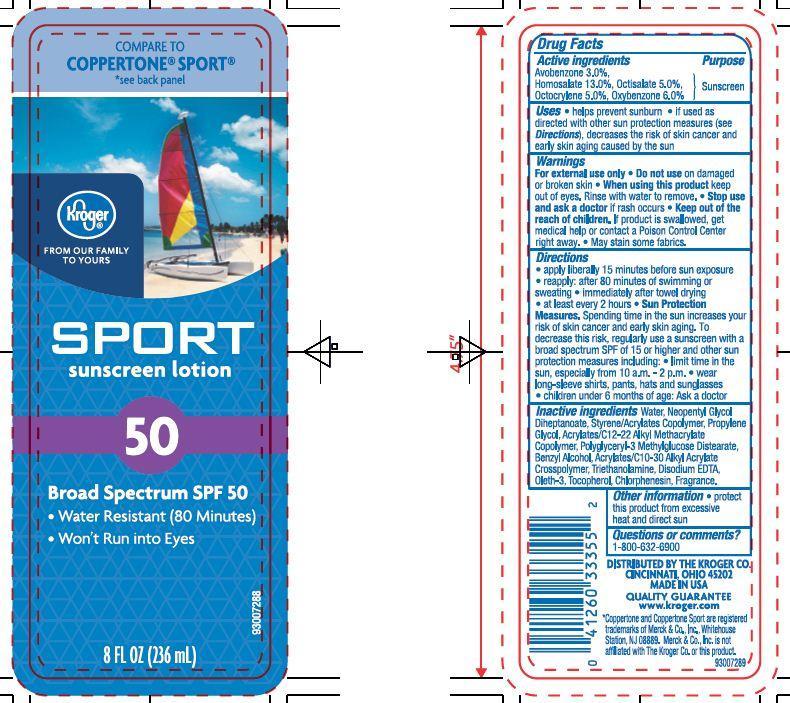 DRUG LABEL: Kroger Sport Sunscreen
NDC: 30142-937 | Form: LOTION
Manufacturer: THE KROGER CO
Category: otc | Type: HUMAN OTC DRUG LABEL
Date: 20140627

ACTIVE INGREDIENTS: AVOBENZONE 3 g/100 g; HOMOSALATE 13 g/100 g; OCTISALATE 5 g/100 g; OCTOCRYLENE 5 g/100 g; OXYBENZONE 6 g/100 g
INACTIVE INGREDIENTS: WATER; NEOPENTYL GLYCOL DIHEPTANOATE; TROLAMINE; BENZYL ALCOHOL; CHLORPHENESIN; OLETH-3; TOCOPHEROL; EDETATE DISODIUM

Drug Facts

Active Ingredients

Avobenzone 3.0 %

Homosalate 13.0%

Octisalate 5.0%

Octocrylene 5.0%

Oxybenzone 6.0%

Purpose

Sunscreen

Uses

- Helps prevent sunburn
- If used as directed with other sun protection measures (see Directions), decrease the risk of skin cancer and early skin aging caused by the sun.

Warnings

For external use only

When using this product

- keep out of eyes. Rinse with water to remove.

Stop use and ask a doctor if

- rash or irritation develops and lasts

keep out of reach of children

If swallowed, get medical help or contact a Poison Control Center right away.

Directions

- apply liberally 15 minutes before sun exposure
- reapply
- after 80 minutes of swimming or sweating
- immediately after towel drying
- at least every 2 hours
- Sun Protection Measures: Spending time in the sun increases your risk of skin cancer and early skin aging. To decrease this risk, regularly use a sunscreen with a broad spectrum SPF of 15 or higher and other sun protection measures including:
- limit time in the sun, especially from 10 a.m. - 2 p.m.
- wear long-sleeve shirts, pants, hats and sunglasses
- children under 6 months of age: Ask a doctor

Other Information

- protect this product from excessive heat and direct sun

Inactive Ingredients

Water, Neopentyl Glycol Diheptanoate, Styrene/Acrylates Copolymer, Propylene Glycol, Polyglyceryl-3 Methylglucose Distearate, Benzyl Alcohol, Acrylates/C10-30 Alkyl Acrylate Crosspolymer, Triethanolamine, Disodium EDTA, Oleth-3, Tocopherol, Chlorphenesin, Fragrance.

Principal Display Panel

COMPARE TO COPPERTONE SPORT

see back panel

kroger

FROM OUR FAMILY TO YOURS

SPORT

sunscreen lotion

50

Broad Spectrum SPF 50

- Water Resistant (80 Minutes)
- Wont Run into Eyes

8 FL OZ (236ml)